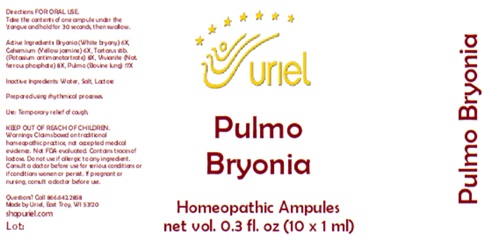 DRUG LABEL: Pulmo Bryonia
NDC: 48951-8084 | Form: LIQUID
Manufacturer: Uriel Pharmacy Inc.
Category: homeopathic | Type: HUMAN OTC DRUG LABEL
Date: 20250801

ACTIVE INGREDIENTS: BRYONIA ALBA ROOT 6 [hp_X]/1 mL; GELSEMIUM SEMPERVIRENS ROOT 6 [hp_X]/1 mL; ANTIMONY POTASSIUM TARTRATE 8 [hp_X]/1 mL; FERROSOFERRIC PHOSPHATE 8 [hp_X]/1 mL; SUS SCROFA LUNG 17 [hp_X]/1 mL
INACTIVE INGREDIENTS: WATER; SODIUM CHLORIDE; LACTOSE

Pulmo Bryonia

INDICATIONS AND USAGE

Directions: FOR ORAL USE.

DOSAGE AND ADMINISTRATION

Take the contents of one ampule under the tongue and hold for 30 seconds, then swallow.

ACTIVE INGREDIENT

Active Ingredients: Bryonia (White bryony) 6X, Gelsemium (Yellow jasmine) 6X, Tartarus stib. (Potassium antimonotartrate) 8X, Vivianite (Nat. ferrous phosphate) 8X, Pulmo (Bovine lung) 17X

Inactive Ingredients: Water, Salt, Lactose

Prepared using rhythmical processes.

PURPOSE

Use: Temporary relief of cough.

KEEP OUT OF REACH OF CHILDREN.

WARNINGS

Warnings: Claims based on traditional homeopathic practice, not accepted medical evidence. Not FDA evaluated. Do not use if allergic to any ingredient. Consult a doctor before use for serious conditions or if conditions worsen or persist. Contains traces of lactose. If pregnant or nursing, consult a doctor before use.

Questions? Call 866.642.2858
Made by Uriel, East Troy, WI 53120
shopuriel.com

Lot: